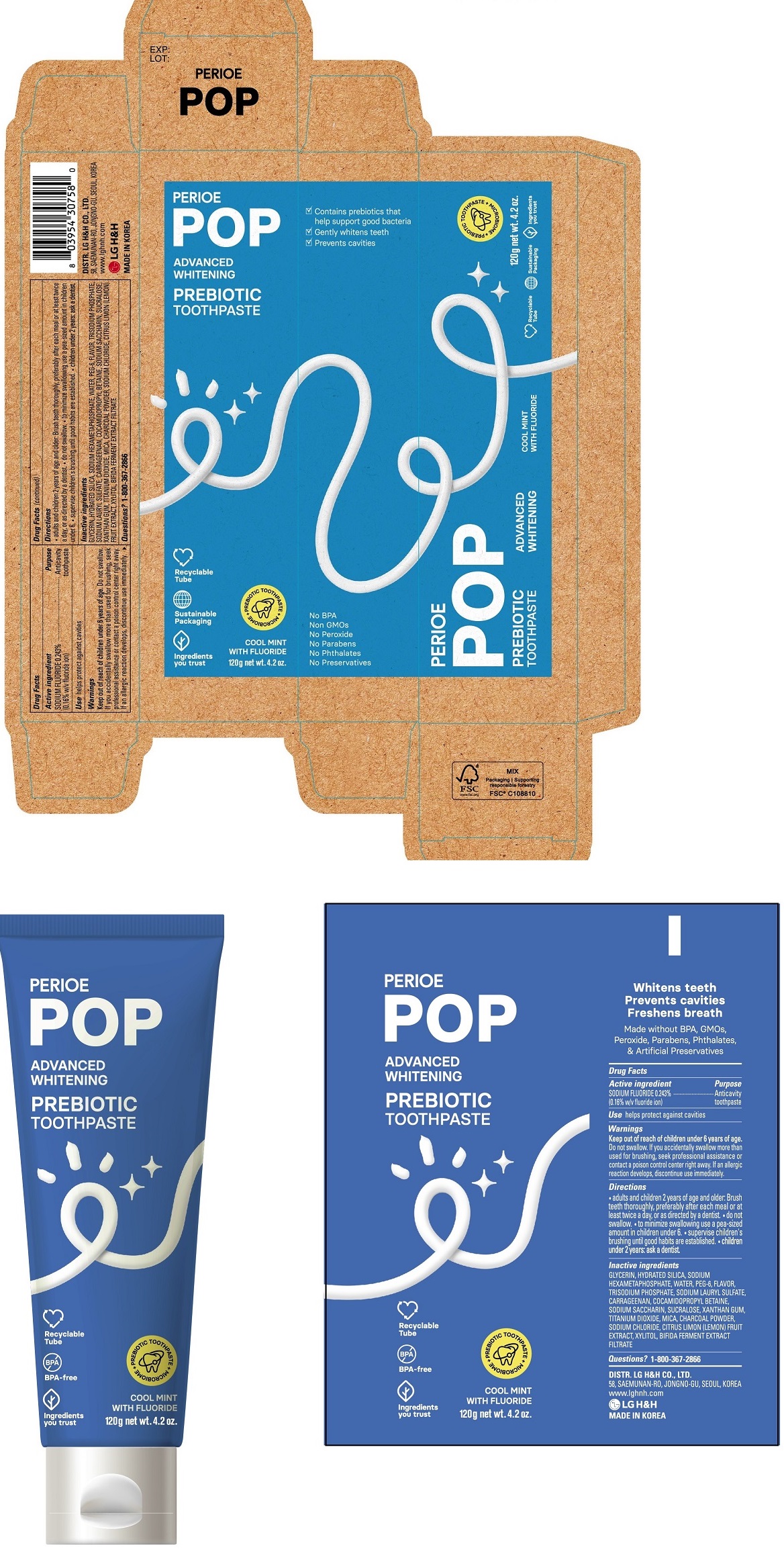 DRUG LABEL: PERIOE POP Advanced Whitening Prebiotic
NDC: 43136-602 | Form: PASTE, DENTIFRICE
Manufacturer: Tai Guk Pharm. Co., Ltd.
Category: otc | Type: HUMAN OTC DRUG LABEL
Date: 20250101

ACTIVE INGREDIENTS: SODIUM FLUORIDE 1.6 mg/1 g
INACTIVE INGREDIENTS: MICA; SUCRALOSE; HYDRATED SILICA; GLYCERIN; WATER; SODIUM POLYMETAPHOSPHATE; CARRAGEENAN; SODIUM LAURYL SULFATE; XYLITOL; SACCHARIN SODIUM; POLYETHYLENE GLYCOL 300; TITANIUM DIOXIDE; ZINC CITRATE; SODIUM CHLORIDE; SODIUM HYDROXIDE; XANTHAN GUM; ACTIVATED CHARCOAL; SODIUM PHOSPHATE, TRIBASIC, ANHYDROUS; COCAMIDOPROPYL BETAINE; LEMON

PERIOE POP Advanced Whitening Prebiotic Toothpaste Cool Mint 120 g

Drug Facts

Active Ingredient

SODIUM FLUORIDE 0.243% (0.16% w/v fluoride ion)

Purpose

Anticavity toothpaste

Use

- helps protect against cavities

Warnings

Keep out of reach of children under 6 years of age.
Do not swallow. If you accidentally swallow more than used for brushing, seek professional assistance or contact a Poison Control Center right away. If an allergic reaction develops, discontinue use immediately.

Directions

- adults and children 2 years of age and older: Brush teeth thoroughly, preferably after each meal or at least twice a day, or as directed by a dentist.
- do not swallow
- to minimize swallowing use a pea-sized amount in children under 6
- supervise children's brushing until good habits are established.
- children under 2 years: ask a dentist.

Inactive Ingredients

GLYCERIN, HYDRATED SILICA, SODIUM HEXAMETAPHOSPHATE, WATER, PEG-6, FLAVOR, TRISODIUM PHOSPHATE, SODIUM LAURYL SULFATE, CARRAGEENAN, COCAMIDOPROPYL BETAINE, SODIUM SACCHARIN, SUCRALOSE, XANTHAN GUM, TITANIUM DIOXIDE, MICA, CHARCOAL POWDER, SODIUM CHLORIDE, CITRUS LIMON (LEMON) FRUIT ETRACT, XYLITOL, BIFIDA FERMENT EXTRACT FILTRATE

Questions?

1-800-367-2866

Distributed by

DISTR. LG H&H CO., LTD.
58, SAEMUNAN-RO, JONGNO-GU, SEOUL, KOREA
www.lghnh.com
LG H&H
MADE IN KOREA

Principal Display Panel - 120 g Tube Carton

PERIOE

POP

ADVANCED
WHITENING

PREBIOTIC
TOOTHPASTE

COOL MINT
WITH FLUORIDE

120g net wt. 4.2 oz.